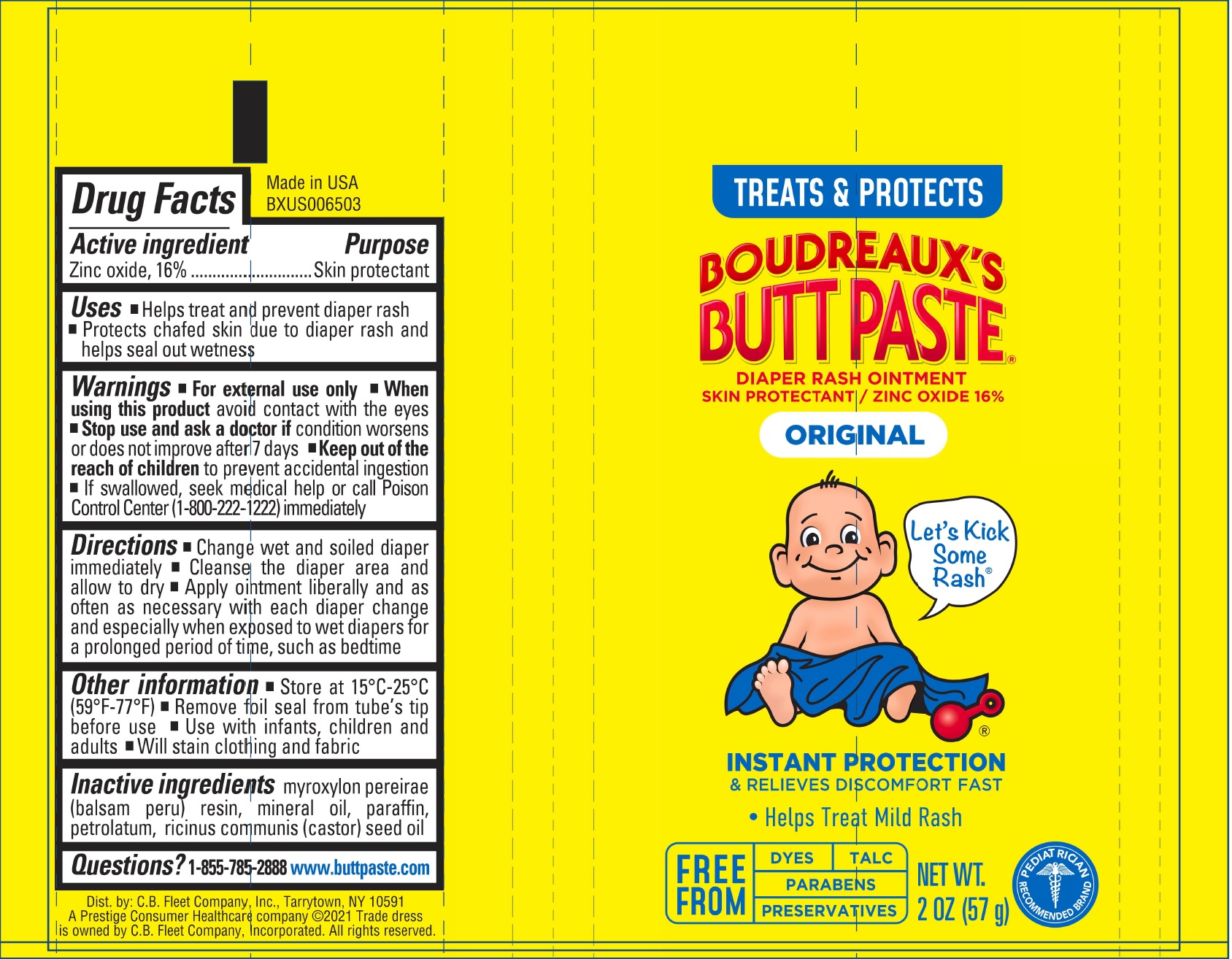 DRUG LABEL: Boudreauxs Butt Diaper Rash Original
NDC: 63471-3002 | Form: CREAM
Manufacturer: Geodis Logistics LLC
Category: otc | Type: HUMAN OTC DRUG LABEL
Date: 20231110

ACTIVE INGREDIENTS: ZINC OXIDE 16 g/113 g
INACTIVE INGREDIENTS: BALSAM PERU; MINERAL OIL; PARAFFIN; PETROLATUM; CASTOR OIL

Boudreaux’s Butt Paste Diaper Rash Ointment Original

Active ingredient

Zinc oxide, 16%

Purpose

Skin protectant

Uses

- Helps treat and prevent diaper rash
- Protects chafed skin due to diaper rash and helps seal out wetness

Warnings

- For external use only

When using this product

- avoid contact with the eyes

Stop use and ask a doctor if

- condition worsens or does not improve after 7 days

Keep out of reach of children

- to prevent accidental ingestion
- If swallowed, seek medical help or call Poison Control Center (1-800-222-1222) immediately

Directions

- Change wet and soiled diaper immediately
- Cleanse the diaper area and allow to dry
- Apply ointment liberally and as often as neessary with each diaper change and especially when exposed to wet diapers for a prolonged period of time, such as bedtime

Other information

- Store at 15°C-25°C (59°F-77°F)
- Remove foil seal from tube's tip before use
- Use with infants, children and adults
- Will stain clothing and fabric

Inactive ingredients

myroxylon pereirae (balsam peru) resin, mineral oil, paraffin, petrolatum, ricinus communis (castor) seed oil

Questions?

1-855-785-2888

www.buttpaste.com